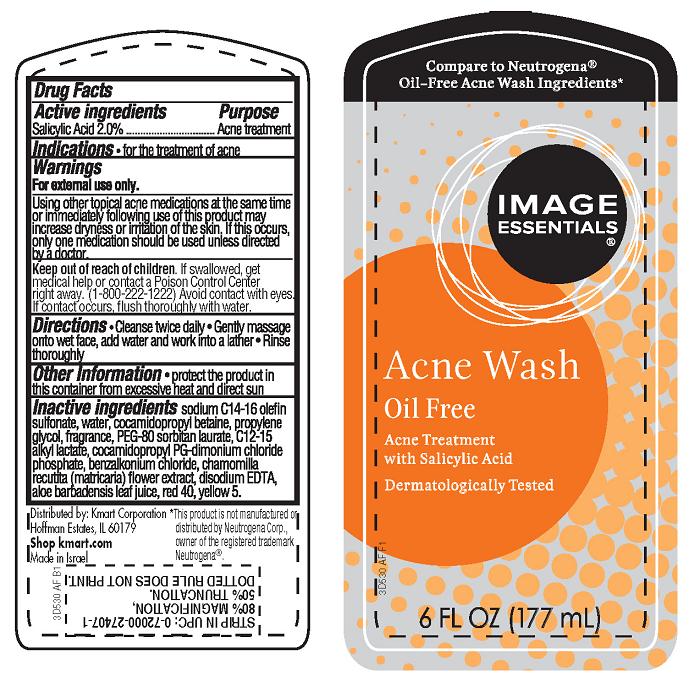 DRUG LABEL: Oil-Free Acne Wash
NDC: 49738-530 | Form: LOTION
Manufacturer: Kmart Corporation
Category: otc | Type: HUMAN OTC DRUG LABEL
Date: 20130729

ACTIVE INGREDIENTS: SALICYLIC ACID 2 g/100 mL
INACTIVE INGREDIENTS: SODIUM C14-16 OLEFIN SULFONATE; WATER; COCAMIDOPROPYL BETAINE; PROPYLENE GLYCOL; POLYETHYLENE GLYCOL 3500; C12-15 ALKYL LACTATE; COCAMIDOPROPYL PG-DIMONIUM CHLORIDE PHOSPHATE; BENZALKONIUM CHLORIDE; EDETATE DISODIUM; CHAMOMILE; ALOE VERA LEAF; FD&C YELLOW NO. 5; FD&C RED NO. 40

Image Essentials® Oil-Free Acne Wash

Active ingredient

Salicylic Acid 2.0%

Purpose

Acne Treatment

Indications

- for the treatment of acne

Warnings

For external use only.

Using other topical acne medications at the same time or immediately following use of this product may increase dryness or irritation of the skin. If this occurs, only one medication should be used unless directed by a doctor.

Keep Out of Reach of Children.

If swallowed, get medical help or contact a Poison Control Center right away. (1-800-222-1222) Avoid contact with eyes. If contact occurs, flush thoroughly with water.

Directions

- Cleanse twice daily
- Gently massage onto wet face, add water and work into a lather
- Rinse thoroughly

Other Information

- Protect the product in this container from excessive heat and direct sun

Inactive ingredients

sodium C14-16 olefin sulfonate, water, cocamidopropyl betaine, propylene glycol, fragrance, PEG-80 sorbitan laurate, C12-15 alkyl lactate, cocamidopropyl PG-dimonium chloride phosphate, benzalkonium chloride, chamomilla recutita (matricaria) flower extract, disodium EDTA, aloe barbadensis leaf juice, red 40, yellow 5.

Package/Label Principal Display Panel

Image Essentials® Acne Wash

Oil-Free

Acne Treatment with Salicylic Acid

Dermatologically Tested

*Compare to Neutrogena® Oil-Free Acne Wash Ingredients

6 Fl Oz (177 mL)

DISTRIBUTED BY:
Kmart Corporation
Hoffman Estates, IL 60179

Shop kmart.com

Made in Israel

*This product is not manufactured or distributed by Neutrogena Corp., owner of the registered trademark Neutrogena®

Bottle Label